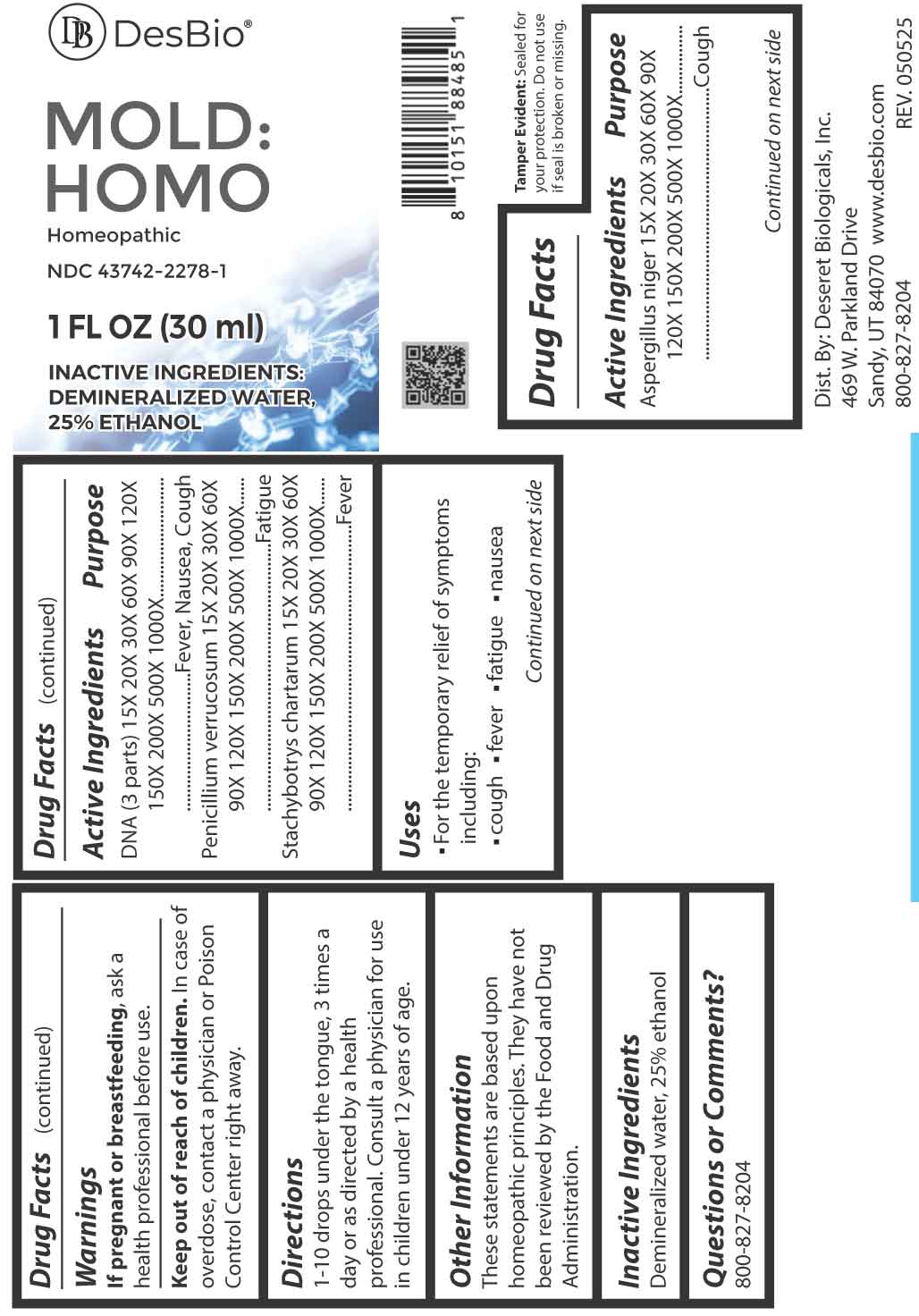 DRUG LABEL: Mold Homo
NDC: 43742-2278 | Form: LIQUID
Manufacturer: Deseret Biologicals, Inc.
Category: homeopathic | Type: HUMAN OTC DRUG LABEL
Date: 20260219

ACTIVE INGREDIENTS: ASPERGILLUS NIGER VAR. NIGER 15 [hp_X]/1 mL; HERRING SPERM DNA 15 [hp_X]/1 mL; PENICILLIUM VERRUCOSUM 15 [hp_X]/1 mL; STACHYBOTRYS CHARTARUM 15 [hp_X]/1 mL
INACTIVE INGREDIENTS: WATER; ALCOHOL

DRUG FACTS:

ACTIVE INGREDIENTS:

Aspergillus Niger 15X, 20X, 30X, 60X, 90X, 120X, 150X, 200X, 500X, 1000X, DNA (3 parts) 15X, 20X, 30X, 60X, 90X, 120X, 150X, 200X, 500X, 1000X, Penicillium Verrucosum 15X, 20X, 30X, 60X, 90X, 120X, 150X, 200X, 500X, 1000X, Stachybotrys Chartarum 15X, 20X, 30X, 60X, 90X, 120X, 150X, 200X, 500X, 1000X.

PURPOSE:

Aspergillus Niger - Cough, DNA (3 parts) – fever, Nausea, Cough, Penicillium Verrucosum - Fatigue, Stachybotrys Chartarum - Fever

USES:

• For the temporary relief of symptoms including:

• cough • fever • fatigue • nausea

These statements are based upon homeopathic principles. They have not been reviewed by the Food and Drug Administration.

WARNINGS:

If pregnant or breastfeeding, ask a health professional before use.

Keep out of reach of children. In case of overdose, contact a physician or Poison Control Center right away.

Tamper Evident: Sealed for your protection. Do not use if seal is broken or missing.

KEEP OUT OF REACH OF CHILDREN:

In case of overdose, contact a physician or Poison Control Center right away.

DIRECTIONS:

1-10 drops under the tongue, 3 times a day or as directed by a health professional. Consult a physician for use in children under 12 years of age.

INACTIVE INGREDIENTS:

Demineralized water, 25% ethanol

QUESTIONS:

Dist. By: Deseret Biologicals, Inc.

469 W. Parkland Drive

Sandy, UT 84070

www.desbio.com

800-827-8204

PACKAGE LABEL DISPLAY:

DesBio

MOLD:HOMO

Homeopathic

NDC 43742-2278-1

1 FL OZ (30 ml)